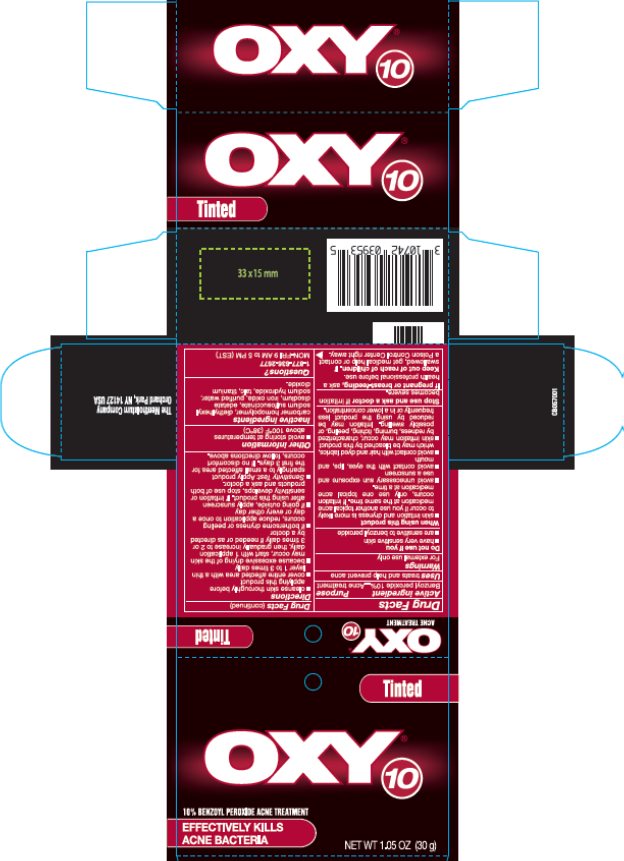 DRUG LABEL: Oxy 10
NDC: 10742-8354 | Form: LOTION
Manufacturer: The Mentholatum Company
Category: otc | Type: HUMAN OTC DRUG LABEL
Date: 20241217

ACTIVE INGREDIENTS: BENZOYL PEROXIDE 100 mg/1 g
INACTIVE INGREDIENTS: CARBOMER HOMOPOLYMER TYPE C (ALLYL PENTAERYTHRITOL CROSSLINKED); DOCUSATE SODIUM; EDETATE DISODIUM; FERRIC OXIDE RED; WATER; SODIUM HYDROXIDE; TALC; TITANIUM DIOXIDE

Drug Facts - Oxy 10 Tinted

Active ingredient

Benzoyl peroxide 10%

Purpose

Acne treatment

Uses

treats and helps prevent acne

Warnings

For external use only

Do Not Use if you

- have very sensitive skin
- are sensitive to benzoyl peroxide

When using this product

- skin irritation and dryness is more likely to occur if you use another topical acne medication at the same time. If irritation occurs, only use one topical acne medication at a time.
- avoid unnecessary sun exposure and use a sunscreen
- avoid contact with the eyes, lips, and mouth
- avoid contact with hair and dyed fabrics, which may be bleached by this product
- skin irritation may occur, characterized by redness, burning, itching, peeling, or possibly swelling. Irritation may be reduced by using this product less frequently or in a lower concentration.

Stop use and ask a doctor if

irritation becomes severe

If pregnant or breast-feeding

Ask a health professional before use.

Keep Out of Reach of Children

If swallowed, get medical help or contact a Poison Control Center right away.

Directions

- clean skin thoroughly before applying this product
- cover entire affected area with a thin layer 1 to 3 times daily
- because excessive drying of the skin may occur, start with 1 application daily, then gradually increase to 2 or 3 times daily if needed or as directed by a doctor
- if bothersome dryness or peeling occurs, reduce application to once a day or every other day
- if going outside, apply sunscreen after using this product. If irritation or sensitivity develops, stop use of both products and ask a doctor.

Inactive Ingredients

carbomer homopolymer, diethylhexyl sodium sulfosuccinate, edetate disodium, iron oxide, purified water, sodium hydroxide, talc, titanium dioxide